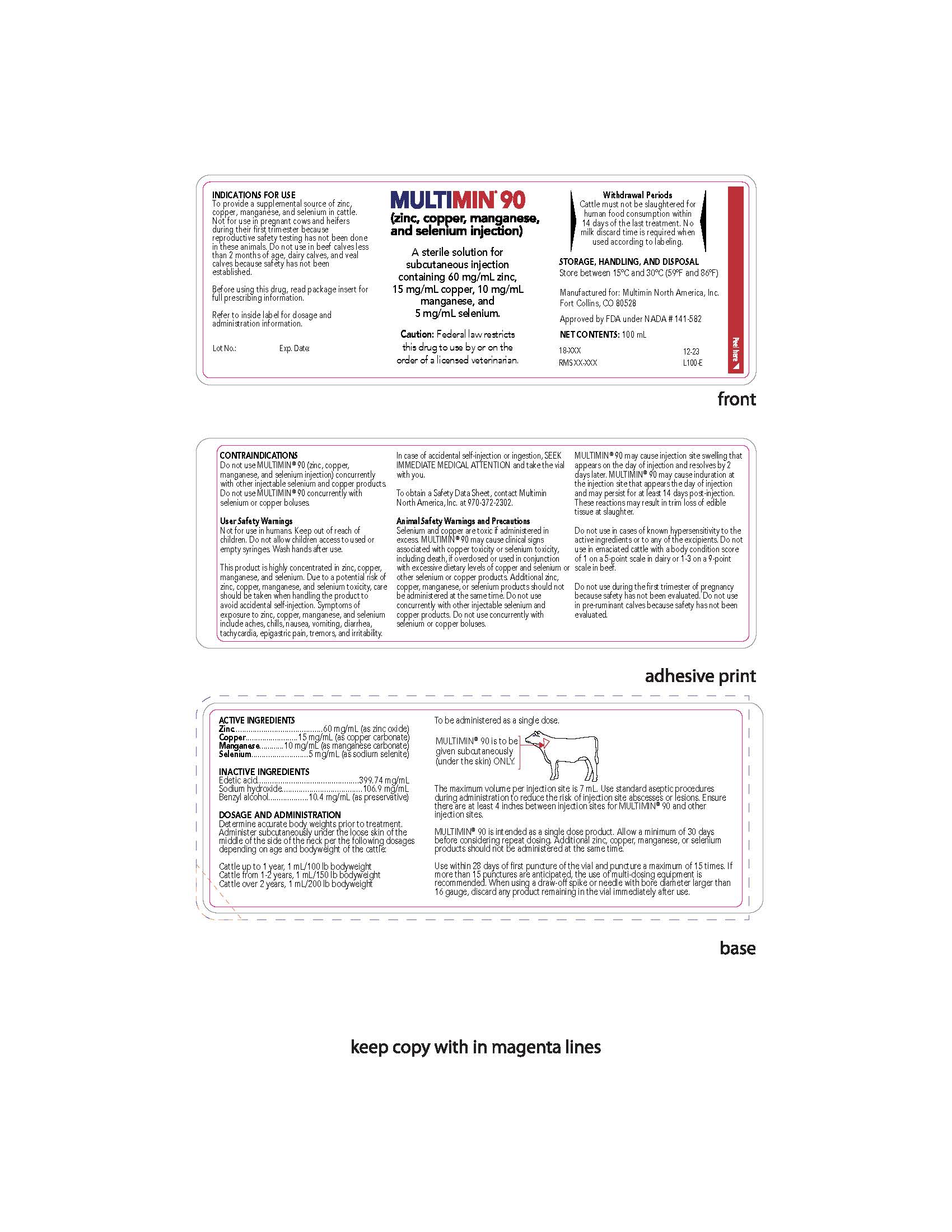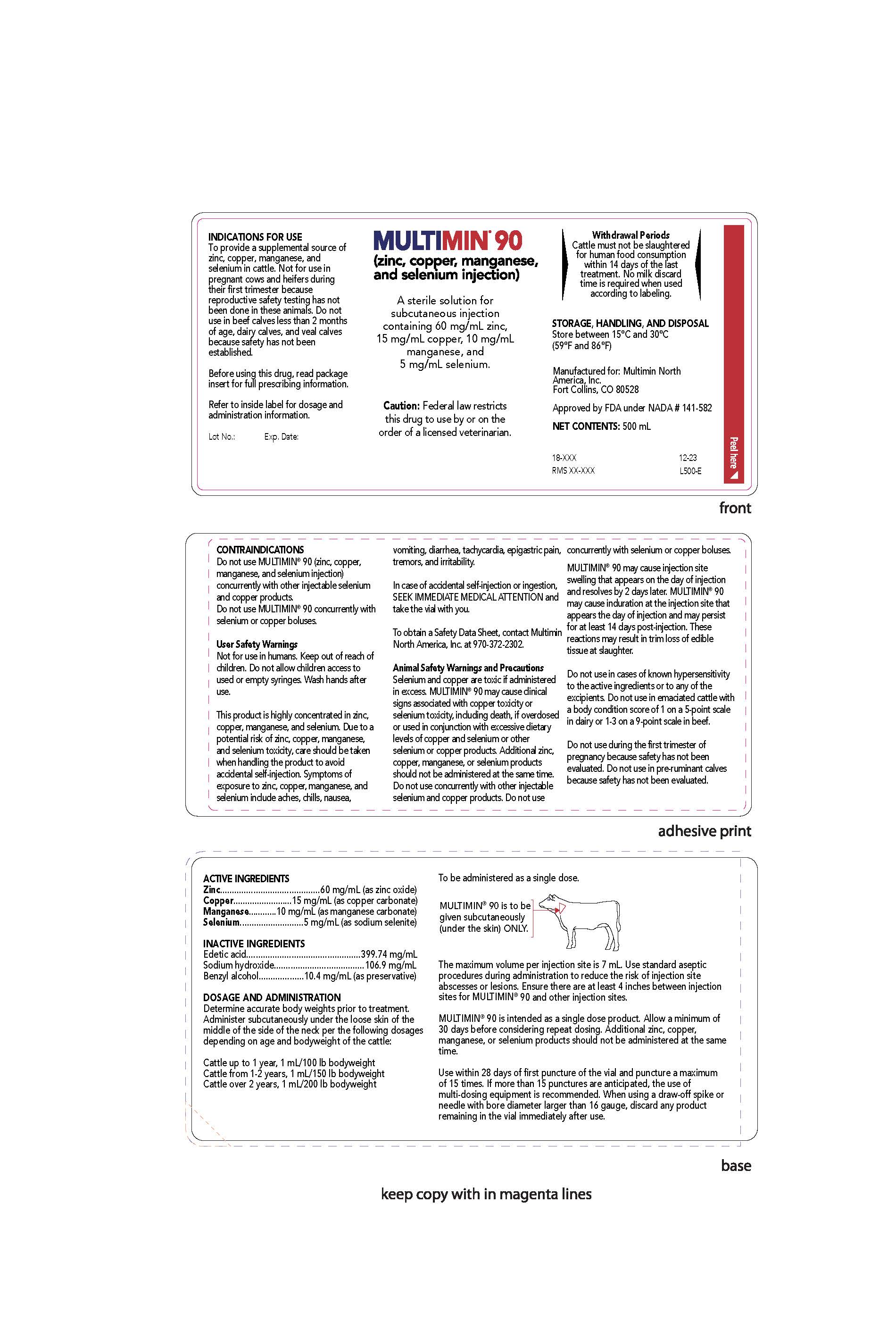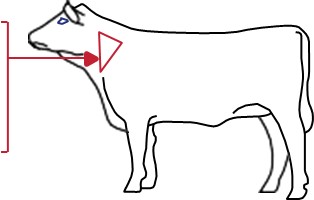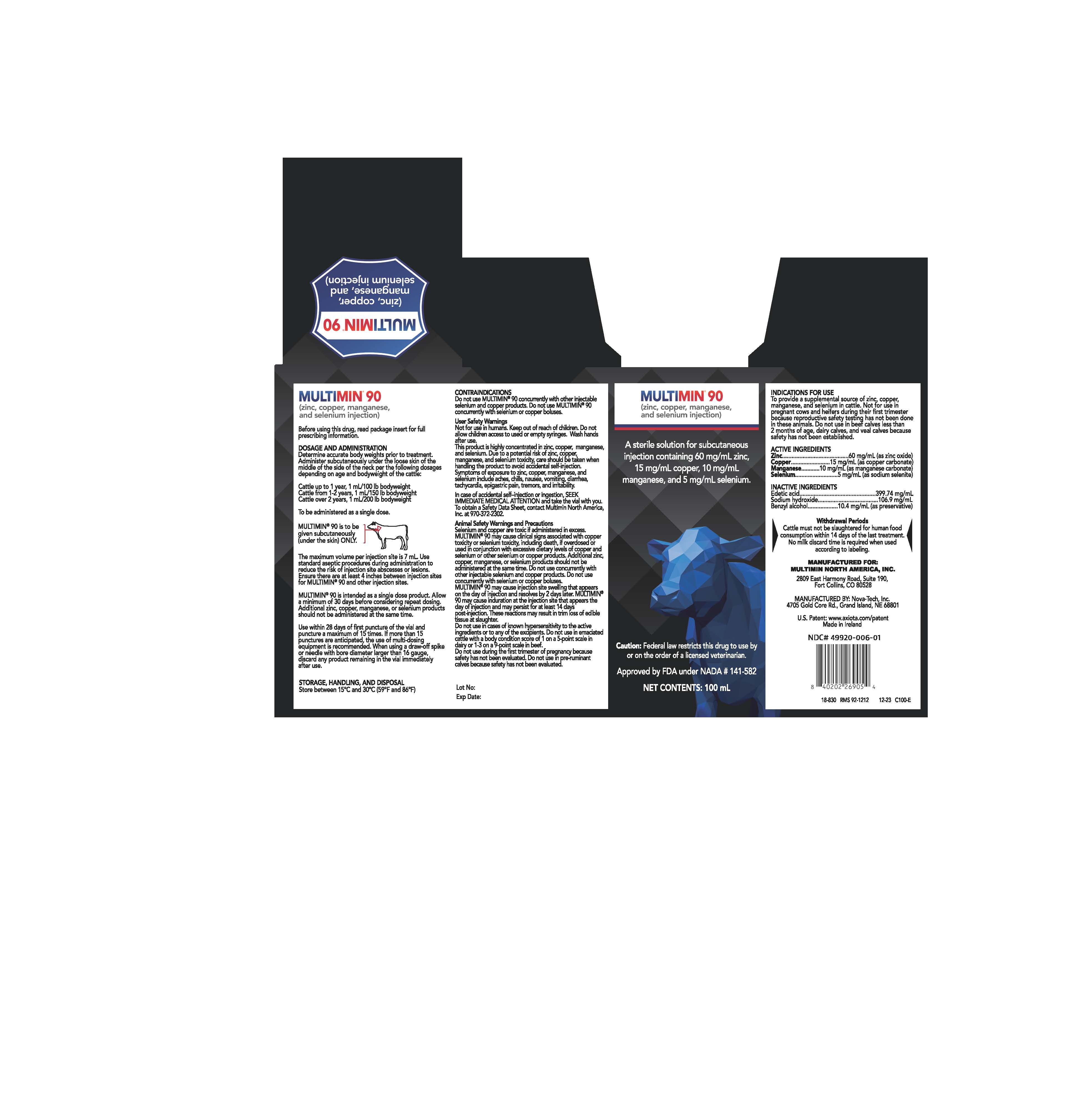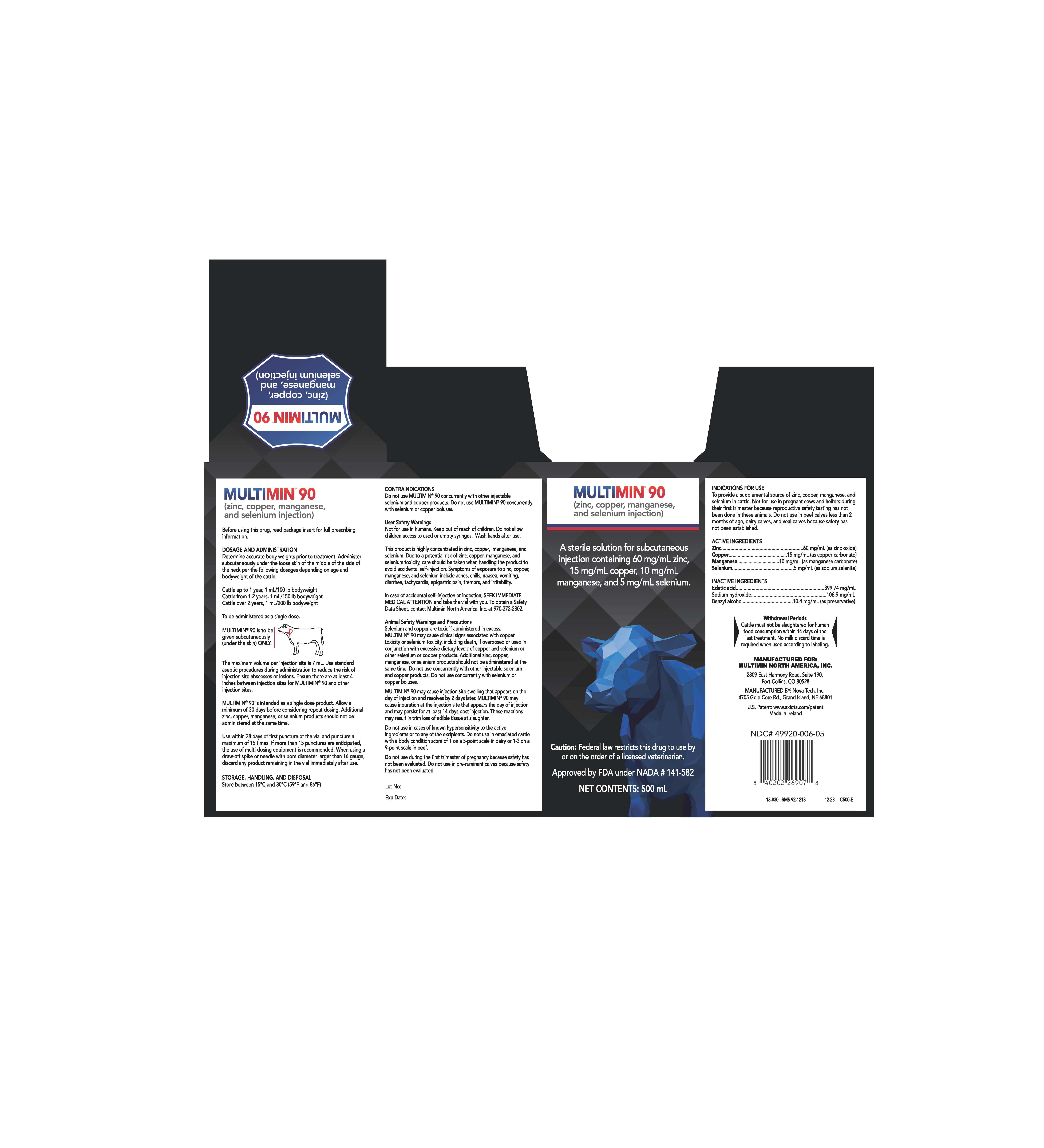 DRUG LABEL: Multimin 90
NDC: 49920-006 | Form: INJECTION, SOLUTION
Manufacturer: Multimin North America, Inc.
Category: animal | Type: PRESCRIPTION ANIMAL DRUG LABEL
Date: 20251105

ACTIVE INGREDIENTS: ZINC OXIDE 60 mg/1 mL; MANGANESE CARBONATE 10 mg/1 mL; SODIUM SELENITE 5 mg/1 mL; CUPRIC CARBONATE 15 mg/1 mL
INACTIVE INGREDIENTS: BENZYL ALCOHOL; SODIUM HYDROXIDE; WATER; EDETIC ACID

MULTIMIN 90

MULTIMIN® 90

(zinc, copper, manganese, and selenium injection)

A sterile solution for subcutaneous injection containing 60 mg/mL zinc, 15 mg/mL copper, 10 mg/mL manganese, and 5 mg/mL selenium.

Caution: Federal law restricts this drug to use by or on the order of a licensed veterinarian.

DESCRIPTION

An injectable blue aqueous sterile solution for subcutaneous injection.

Active Ingredients:
Zinc 60 mg/mL (as zinc oxide)
Copper 15 mg/mL (as copper carbonate)
Manganese 10 mg/mL (as manganese carbonate)
Selenium 5 mg/mL (as sodium selenite)

Inactive Ingredients:
Edetic acid 399.74 mg/mL
Sodium hydroxide 106.9 mg/mL
Benzyl alcohol 10.4 mg/mL (as preservative)

INDICATIONS FOR USE

To provide a supplemental source of zinc, copper, manganese, and selenium in cattle. Not for use in pregnant cows and heifers during their first trimester because reproductive safety testing has not been done in these animals. Do not use in beef calves less than 2 months of age, dairy calves, and veal calves because safety has not been established.

DOSAGE AND ADMINISTRATION

Determine accurate body weights prior to treatment. Administer subcutaneously under the loose skin of the middle of the side of the neck per the following dosages depending on age and bodyweight of the cattle:

Cattle up to 1 year, 1 mL/100 lb bodyweight
Cattle from 1-2 years, 1 mL/150 lb bodyweight
Cattle over 2 years, 1 mL/200 lb bodyweight

To be administered as a single dose.

MULTIMIN® 90 is to be given subcutaneously (under the skin) ONLY.

The maximum volume per injection site is 7 mL. Use standard aseptic procedures during administration to reduce the risk of injection site abscesses or lesions. Ensure there are at least 4 inches between injection sites for MULTIMIN® 90 and other injection sites.

MULTIMIN® 90 is intended as a single dose product. Allow a minimum of 30 days before considering repeat dosing. Additional zinc, copper, manganese, or selenium products should not be administered at the same time.

Use within 28 days of first puncture of the vial and puncture a maximum of 15 times. If more than 15 punctures are anticipated, the use of multi-dosing equipment is recommended. When using a draw-off spike or needle with bore diameter larger than 16 gauge, discard any product remaining in the vial immediately after use.

CONTRAINDICATIONS

Do not use MULTIMIN® 90 (zinc, copper,
manganese, and selenium injection)
concurrently with other injectable selenium
and copper products.
Do not use MULTIMIN® 90 concurrently with
selenium or copper boluses.

WARNINGS AND PRECAUTIONS

Withdrawal Periods
Cattle must not be slaughtered for human food consumption within 14 days of the last treatment. No milk discard time is required when used according to labeling.

User Safety Warnings

Not for use in humans. Keep out of reach of children. Do not allow children access to used or empty syringes. Wash hands after use.

This product is highly concentrated in zinc, copper, manganese, and selenium. Due to a potential risk of zinc, copper, manganese, and selenium toxicity, care should be taken when handling the product to avoid accidental self-injection. Symptoms of exposure to zinc, copper, manganese, and selenium include aches, chills, nausea, vomiting, diarrhea, tachycardia, epigastric pain, tremors, and irritability.

In case of accidental self-injection or ingestion, SEEK IMMEDIATE MEDICAL ATTENTION and take the vial with you.

To obtain a Safety Data Sheet, contact Multimin North America, Inc. at 970-372-2302.

Animal Safety Warnings and Precautions

Selenium and copper are toxic if administered in excess. MULTIMIN® 90 may cause clinical signs associated with copper toxicity or selenium toxicity, including death, if overdosed or used in conjunction with excessive dietary levels of copper and selenium or other selenium or copper products. Additional zinc, copper, manganese, or selenium products should not be administered at the same time. Do not use concurrently with other injectable selenium and copper products. Do not use concurrently with selenium or copper boluses.

MULTIMIN® 90 may cause injection site swelling that appears on the day of injection and resolves by 2 days later. MULTIMIN® 90 may cause induration at the injection site that appears the day of injection and may persist for at least 14 days post-injection. These reactions may result in trim loss of edible tissue at slaughter.

Do not use in cases of known hypersensitivity to the active ingredients or to any of the excipients. Do not use in emaciated cattle with a body condition score of 1 on a 5-point scale in dairy or 1-3 on a 9-point scale in beef.

Do not use during the first trimester of pregnancy because safety has not been evaluated. Do not use in pre-ruminant calves because safety has not been evaluated.

ADVERSE REACTIONS

Accidental overdose of copper or selenium through misdosing or the use of multiple sources, including the use of injectable products in addition to high dietary levels, can result in adverse events, including death, depression, weakness, ataxia, salivation, and drooling.

CONTACT INFORMATION

Contact Multimin North America, Inc. at 970-372-2302 or http://www.axiota.com. To report suspected adverse drug experiences, contact Multimin North America, Inc. at 970-372-2302. For additional information about reporting adverse drug experiences for animal drugs, contact FDA at 1-888-FDA-VETS (1-888-332-8387) or http://www.fda.gov/reportanimalae

CLINICAL PHARMACOLOGY

As essential minerals, zinc, copper, manganese, and selenium, contribute to homeostasis by participating as cofactors of a wide range of enzymes in multiple biochemical processes in the body. In a laboratory margin of safety study in 32 growing cattle less than 1 year of age, after daily subcutaneous administration of MULTIMIN® 90 (zinc, copper, manganese, and selenium injection) for 3 days (see Target Animal Safety section), a dose-related increase in plasma concentrations of zinc, copper, manganese, and selenium was observed for treated animals when compared with untreated controls.

TARGET ANIMAL SAFETY

MULTIMIN® 90 or saline was injected subcutaneously over 3 consecutive days to 32 English and/or Continental pure or mixed beef breed cattle (16 non-pregnant females and 16 intact males, 4 animals per sex per treatment group) ranging in weight from 289-387 kg and less than 10 months of age. Treatment groups were 1x [1 mL MULTIMIN® 90/100 lb (45 kg) body weight (BW)], 3x [3 mL MULTIMIN® 90/100 lb (45 kg) BW], 5x [5 mL MULTIMIN® 90/100 lb (45 kg) BW], or control group [5 mL saline/100 lb (45 kg) BW]. All animals were euthanized and necropsied 1 to 2 days after the last treatment. The only treatment-associated findings from the 1x dose group included injection site swelling and a minor, clinically insignificant, dose and time dependent decrease in cholesterol. The treatment-associated findings from the 3x dose group were injection site swelling, a decrease in feed consumption, and a decrease in cholesterol. In the 5x dose group, treatment-associated findings included injection site swelling, a decrease in feed consumption, a decrease in cholesterol, an increase in creatinine kinase, a decrease in calcium, and signs of acute copper toxicity (2 out of 8 animals), including sudden death, depression, weakness, ataxia, salivation, and drooling. Animals in the 5x dose group also had hepatic centrilobular necrosis on necropsy and an increase in serum chemistries associated with liver damage.

Sixteen animals were each injected with MULTIMIN® 90 and saline subcutaneously on opposite sides of the neck. Eleven animals were administered 1 mL/50 kg body weight and the other 5 animals received the maximum dose per injection site of 7 mL. Injection of MULTIMIN® 90 resulted in pain upon injection (1 of 16 animals); injection site swelling that appeared on the day of injection and resolved 2 days later; and induration that appeared on the day of injection and persisted for at least 14 days. Subcutaneous injection of MULTIMIN® 90 in cattle can cause a local tissue reaction. These reactions may result in trim loss of edible tissue at slaughter.

EFFECTIVENESS

To provide a supplemental source of zinc, copper, manganese, and selenium was demonstrated in a single multisite study. A total of 90 Holstein replacement dairy heifers, approximately 9 months of age, were administered either a single subcutaneous injection of MULTIMIN® 90 or saline at a dose of 1 mL/100 lb (45 kg) BW on Day 0. Blood samples were obtained for plasma zinc, copper, manganese, and selenium analysis within 1 to 2 hours prior to dosing, and 0.5 hours (± 10 minutes), 1 hour (± 10 minutes), 3 hours (± 15 minutes), 6 hours (± 15 minutes), and 8 hours (± 15 minutes) post-treatment. Treatment was considered successful if the partial area under the plasma concentration curve from dosing to 8 hours (AUC0-8) of zinc, copper, manganese, and selenium was significantly different and higher in the MULTIMIN® 90 treated group versus the saline treated group. For all four minerals the AUC0-8 was different and higher in the MULTIMIN® 90 treated group versus the saline treated group. The mean AUC0-8 for zinc plasma concentration was significantly different and higher (P-value=0.0031) in the MULTIMIN® 90 treated group (16.36 hour*mg/L) compared to the saline treated group (7.74 hour*mg/L). The mean AUC0-8 for copper plasma concentration was significantly different and higher (P-value=0.0041) in the MULTIMIN® 90 treated group (8.34 hour*mg/L) compared to the saline treated group (7.05 hour*mg/L). The mean AUC0-8 for manganese plasma concentration was significantly different and higher (P-value=0.0023) in the MULTIMIN® 90 treated group (253.79 hour*μg/L) compared to the saline treated group (10.89 hour*μg/L). The mean AUC0-8 for selenium plasma concentration was significantly different and higher (P-value=0.0042) in the MULTIMIN® 90 treated group (2734.03 hour*μg/L) compared to the saline treated group (790.25 hour*μg/L).

HOW SUPPLIED

MULTIMIN® 90 is available in the following package sizes:
100 mL vial
500 mL vial

NDC# 49920-006-01
NDC# 49920-006-05

STORAGE, HANDLING, AND DISPOSAL

Store between 15°C and 30°C (59°F and 86°F).

Approved by FDA under NADA # 141-582

NAME AND PLACE OF BUSINESS

Manufactured for: Multimin North America, Inc.,
2809 East Harmony Rd. Suite 190, Fort Collins, CO 80528
Manufactured by: Nova-Tech, Inc.,
4705 Gold Core Rd., Grand Island, NE, 68801

U.S. Patent: www.axiota.com/patent

Made in Ireland

REVISION DATE
December 2023

Package Label Principle Display Panel

MULTIMIN® 90

(zinc, copper, manganese, and selenium injection)

A sterile solution for
subcutaneous injection
containing 60 mg/mL zinc,
15 mg/mL copper, 10 mg/mL
manganese, and
5 mg/mL selenium.

Caution: Federal law restricts
this drug to use by or on the
order of a licensed veterinarian.

Withdrawal periods

Cattle must not be slaughtered for human food

consumption within 14 days of the last treatment.

No milk discard time is required when used according to labeling.

STORAGE, HANDLING, AND DISPOSAL
Store between 15ºC and 30ºC
(59ºF and 86ºF)

Manufactured for: Multimin North
America, Inc.
Fort Collins, CO 80528

Approved by FDA under NADA # 141-582

NET CONTENTS: 100mL

INDICATIONS FOR USE

To provide a supplemental source of
zinc, copper, manganese, and
selenium in cattle. Not for use in
pregnant cows and heifers during
their first trimester because
reproductive safety testing has not
been done in these animals. Do not
use in beef calves less than 2 months
of age, dairy calves, and veal calves
because safety has not been
established.
Before using this drug, read package
insert for full prescribing information.
Refer to inside label for dosage and
administration information.

Lot No.: Exp. Date:

CONTRAINDICATIONS
Do not use MULTIMIN® 90 (zinc, copper,
manganese, and selenium injection) concurrently
with other injectable selenium and copper products.
Do not use MULTIMIN® 90 concurrently with
selenium or copper boluses.

User Safety Warnings
Not for use in humans. Keep out of reach of
children. Do not allow children access to used or
empty syringes. Wash hands after use.
This product is highly concentrated in zinc, copper,
manganese, and selenium. Due to a potential risk of
zinc, copper, manganese, and selenium toxicity, care
should be taken when handling the product to
avoid accidental self-injection. Symptoms of
exposure to zinc, copper, manganese, and selenium
include aches, chills, nausea, vomiting, diarrhea,
tachycardia, epigastric pain, tremors, and irritability.

In case of accidental self-injection or ingestion, SEEK
IMMEDIATE MEDICAL ATTENTION and take the vial
with you.
To obtain a Safety Data Sheet, contact Multimin
North America, Inc. at 970-372-2302.

Animal Safety Warnings and Precautions
Selenium and copper are toxic if administered in
excess. MULTIMIN® 90 may cause clinical signs
associated with copper toxicity or selenium toxicity,
including death, if overdosed or used in conjunction
with excessive dietary levels of copper and selenium or
other selenium or copper products. Additional zinc,
copper, manganese, or selenium products should not
be administered at the same time. Do not use
concurrently with other injectable selenium and
copper products. Do not use concurrently with
selenium or copper boluses.

MULTIMIN® 90 may cause injection site swelling that
appears on the day of injection and resolves by 2
days later. MULTIMIN® 90 may cause induration at
the injection site that appears the day of injection
and may persist for at least 14 days post-injection.
These reactions may result in trim loss of edible
tissue at slaughter.

Do not use in cases of known hypersensitivity to the
active ingredients or to any of the excipients. Do not
use in emaciated cattle with a body condition score
of 1 on a 5-point scale in dairy or 1-3 on a 9-point
scale in beef.

Do not use during the first trimester of pregnancy
because safety has not been evaluated. Do not use
in pre-ruminant calves because safety has not been
evaluated.

ACTIVE INGREDIENTS
Zinc..........................................60 mg/mL (as zinc oxide)
Copper.........................15 mg/mL (as copper carbonate)
Manganese............10 mg/mL (as manganese carbonate)
Selenium...........................5 mg/mL (as sodium selenite)

INACTIVE INGREDIENTS
Edetic acid................................................399.74 mg/mL
Sodium hydroxide......................................106.9 mg/mL
Benzyl alcohol...................10.4 mg/mL (as preservative)

DOSAGE AND ADMINISTRATION
Determine accurate body weights prior to treatment.
Administer subcutaneously under the loose skin of the
middle of the side of the neck per the following dosages
depending on age and bodyweight of the cattle:
Cattle up to 1 year, 1 mL/100 lb bodyweight
Cattle from 1-2 years, 1 mL/150 lb bodyweight
Cattle over 2 years, 1 mL/200 lb bodyweight

To be administered as a single dose.

MULTIMIN® 90 is to be
given subcutaneously
(under the skin) ONLY.

The maximum volume per injection site is 7 mL. Use standard aseptic procedures
during administration to reduce the risk of injection site abscesses or lesions. Ensure
there are at least 4 inches between injection sites for MULTIMIN® 90 and other
injection sites.

MULTIMIN® 90 is intended as a single dose product. Allow a minimum of 30 days
before considering repeat dosing. Additional zinc, copper, manganese, or selenium
products should not be administered at the same time.

Use within 28 days of first puncture of the vial and puncture a maximum of 15 times. If
more than 15 punctures are anticipated, the use of multi-dosing equipment is
recommended. When using a draw-off spike or needle with bore diameter larger than
16 gauge, discard any product remaining in the vial immediately after use.

Package Label Principle Display Panel

MULTIMIN® 90

(zinc, copper, manganese, and selenium injection)

A sterile solution for
subcutaneous injection
containing 60 mg/mL zinc,
15 mg/mL copper, 10 mg/mL
manganese, and
5 mg/mL selenium.

Caution: Federal law restricts
this drug to use by or on the
order of a licensed veterinarian.

Withdrawal periods

Cattle must not be slaughtered for human food

consumption within 14 days of the last treatment.

No milk discard time is required when used according to labeling.

STORAGE, HANDLING, AND DISPOSAL
Store between 15ºC and 30ºC
(59ºF and 86ºF)

Manufactured for: Multimin North
America, Inc.
Fort Collins, CO 80528

Approved by FDA under NADA # 141-582

NET CONTENTS: 500mL

INDICATIONS FOR USE

To provide a supplemental source of
zinc, copper, manganese, and
selenium in cattle. Not for use in
pregnant cows and heifers during
their first trimester because
reproductive safety testing has not
been done in these animals. Do not
use in beef calves less than 2 months
of age, dairy calves, and veal calves
because safety has not been
established.
Before using this drug, read package
insert for full prescribing information.
Refer to inside label for dosage and
administration information.

Lot No.: Exp. Date:

CONTRAINDICATIONS
Do not use MULTIMIN® 90 (zinc, copper,
manganese, and selenium injection) concurrently
with other injectable selenium and copper products.
Do not use MULTIMIN® 90 concurrently with
selenium or copper boluses.

User Safety Warnings
Not for use in humans. Keep out of reach of
children. Do not allow children access to used or
empty syringes. Wash hands after use.
This product is highly concentrated in zinc, copper,
manganese, and selenium. Due to a potential risk of
zinc, copper, manganese, and selenium toxicity, care
should be taken when handling the product to
avoid accidental self-injection. Symptoms of
exposure to zinc, copper, manganese, and selenium
include aches, chills, nausea, vomiting, diarrhea,
tachycardia, epigastric pain, tremors, and irritability.

In case of accidental self-injection or ingestion, SEEK
IMMEDIATE MEDICAL ATTENTION and take the vial
with you.

To obtain a Safety Data Sheet, contact Multimin
North America, Inc. at 970-372-2302.

Animal Safety Warnings and Precautions
Selenium and copper are toxic if administered in
excess. MULTIMIN® 90 may cause clinical signs
associated with copper toxicity or selenium toxicity,
including death, if overdosed or used in conjunction
with excessive dietary levels of copper and selenium or
other selenium or copper products. Additional zinc,
copper, manganese, or selenium products should not
be administered at the same time. Do not use
concurrently with other injectable selenium and
copper products. Do not use concurrently with
selenium or copper boluses.

MULTIMIN® 90 may cause injection site swelling that
appears on the day of injection and resolves by 2
days later. MULTIMIN® 90 may cause induration at
the injection site that appears the day of injection
and may persist for at least 14 days post-injection.
These reactions may result in trim loss of edible
tissue at slaughter.

Do not use in cases of known hypersensitivity to the
active ingredients or to any of the excipients. Do not
use in emaciated cattle with a body condition score
of 1 on a 5-point scale in dairy or 1-3 on a 9-point
scale in beef.

Do not use during the first trimester of pregnancy
because safety has not been evaluated. Do not use
in pre-ruminant calves because safety has not been
evaluated.

ACTIVE INGREDIENTS
Zinc..........................................60 mg/mL (as zinc oxide)
Copper.........................15 mg/mL (as copper carbonate)
Manganese............10 mg/mL (as manganese carbonate)
Selenium...........................5 mg/mL (as sodium selenite)

INACTIVE INGREDIENTS
Edetic acid................................................399.74 mg/mL
Sodium hydroxide......................................106.9 mg/mL
Benzyl alcohol...................10.4 mg/mL (as preservative)

DOSAGE AND ADMINISTRATION
Determine accurate body weights prior to treatment.
Administer subcutaneously under the loose skin of the
middle of the side of the neck per the following dosages
depending on age and bodyweight of the cattle:

Cattle up to 1 year, 1 mL/100 lb bodyweight
Cattle from 1-2 years, 1 mL/150 lb bodyweight
Cattle over 2 years, 1 mL/200 lb bodyweight

To be administered as a single dose.

MULTIMIN® 90 is to be
given subcutaneously
(under the skin) ONLY.

The maximum volume per injection site is 7 mL. Use standard aseptic procedures
during administration to reduce the risk of injection site abscesses or lesions. Ensure
there are at least 4 inches between injection sites for MULTIMIN® 90 and other
injection sites.

MULTIMIN® 90 is intended as a single dose product. Allow a minimum of 30 days
before considering repeat dosing. Additional zinc, copper, manganese, or selenium
products should not be administered at the same time.

Use within 28 days of first puncture of the vial and puncture a maximum of 15 times. If
more than 15 punctures are anticipated, the use of multi-dosing equipment is
recommended. When using a draw-off spike or needle with bore diameter larger than
16 gauge, discard any product remaining in the vial immediately after use.

Carton 100 ml

MULTIMIN® 90

(zinc, copper, manganese, and selenium injection)

Before using this drug, read package insert for full prescribing information.

Determine accurate body weights prior to treatment. Administer subcutaneously under the loose skin of the middle of the side of the neck per the following dosages depending on age and bodyweight of the cattle:

Cattle up to 1 year, 1 mL/100 lb bodyweight
Cattle from 1-2 years, 1 mL/150 lb bodyweight
Cattle over 2 years, 1 mL/200 lb bodyweight

To be administered as a single dose.

MULTIMIN® 90 is to be given subcutaneously (under the skin) ONLY.

The maximum volume per injection site is 7 mL. Use standard aseptic procedures during administration to reduce the risk of injection site abscesses or lesions. Ensure there are at least 4 inches between injection sites for MULTIMIN® 90 and other injection sites.

MULTIMIN® 90 is intended as a single dose product. Allow a minimum of 30 days before considering repeat dosing. Additional zinc, copper, manganese, or selenium products should not be administered at the same time.

Use within 28 days of first puncture of the vial and puncture a maximum of 15 times. If more than 15 punctures are anticipated, the use of multi-dosing equipment is recommended. When using a draw-off spike or needle with bore diameter larger than 16 gauge, discard any product remaining in the vial immediately after use.

MULTIMIN® 90 is intended as a single dose product. Allow a minimum of 30 days before considering repeat dosing. Additional zinc, copper, manganese, or selenium products should not be administered at the same time.
Use within 28 days of first puncture of the vial and puncture a maximum of 15 times. If more than 15 punctures are anticipated, the use of multi-dosing equipment is recommended. When using a draw-off spike or needle with bore diameter larger than 16 gauge, discard any product remaining in the vial immediately after use.

STORAGE, HANDLING AND DISPOSAL
Store between 15ºC and 30ºC (59ºF and 86ºF)

CONTRAINDICATIONS
Do not use MULTIMIN® 90 (zinc, copper, manganese, and selenium injection) concurrently with other injectable selenium and copper products.
Do not use MULTIMIN® 90 concurrently with selenium or copper boluses.

User Safety Warnings
Not for use in humans. Keep out of reach of children. Do not allow children access to used or empty syringes. Wash hands after use.

This product is highly concentrated in zinc, copper, manganese, and selenium. Due to a potential risk of zinc, copper, manganese, and selenium toxicity, care should be taken when handling the product to avoid accidental self-injection. Symptoms of exposure to zinc, copper, manganese, and selenium include aches, chills, nausea, vomiting, diarrhea, tachycardia, epigastric pain, tremors, and irritability.

In case of accidental self-injection or ingestion, SEEK IMMEDIATE MEDICAL ATTENTION and take the vial with you.
To obtain a Safety Data Sheet, contact Multimin North America, Inc. at 970-372-2302.

Animal Safety Warnings and Precautions
Selenium and copper are toxic if administered in excess. MULTIMIN® 90 may cause clinical signs associated with copper toxicity or selenium toxicity, including death, if overdosed or used in conjunction with excessive dietary levels of copper and selenium or other selenium or copper products. Additional zinc, copper, manganese, or selenium products should not be administered at the same time. Do not use concurrently with other injectable selenium and copper products. Do not use concurrently with selenium or copper boluses.
MULTIMIN® 90 may cause injection site swelling that appears on the day of injection and resolves by 2 days later. MULTIMIN® 90 may cause induration at the injection site that appears the day of injection and may persist for at least 14 days post-injection. These reactions may result in trim loss of edible tissue at slaughter.
Do not use in cases of known hypersensitivity to the active ingredients or to any of the excipients. Do not use in emaciated cattle with a body condition score of 1 on a 5-point scale in dairy or 1-3 on a 9-point scale in beef.
Do not use during the first trimester of pregnancy because safety has not been evaluated. Do not use in pre-ruminant calves because safety has not been evaluated.

Lot No:

Exp Date:

MULTIMIN® 90
(zinc, copper, manganese, and selenium injection)

A sterile solution for subcutaneous injection containing 60 mg/mL zinc, 15 mg/mL copper, 10 mg/mL manganese, and 5 mg/mL selenium.

Caution: Federal law restricts this drug to use by or on the order of a licensed veterinarian.

Approved by FDA under NADA # 141-582

NET CONTENTS: 100 mL

INDICATIONS FOR USE
To provide a supplemental source of zinc, copper, manganese, and selenium in cattle. Not for use in pregnant cows and heifers during their first trimester because reproductive safety testing has not been done in these animals. Do not use in beef calves less than 2 months of age, dairy calves, and veal calves because safety has not been established.

ACTIVE INGREDIENTS:
Zinc 60 mg/mL (as zinc oxide)
Copper 15 mg/mL (as copper carbonate)
Manganese 10 mg/mL (as manganese carbonate)
Selenium 5 mg/mL (as sodium selenite)

INACTIVE INGREDIENTS:
Edetic acid 399.74 mg/mL
Sodium hydroxide 106.9 mg/mL
Benzyl alcohol 10.4 mg/mL (as preservative)

Withdrawal Periods
Cattle must not be slaughtered for human food consumption within 14 days of the last treatment. No milk discard time is required when used according to labeling.

MANUFACTURED FOR:MULTIMIN NORTH AMERICA,INC.
2809 East Harmony Rd. Suite 190, Fort Collins, CO 80528
Manufactured by: Nova-Tech, Inc.,
4705 Gold Core Rd., Grand Island, NE, 68801

U.S. Patent: www.axiota.com/patent
Made in Ireland

NDC#49920-006-05

Carton 500 ml

MULTIMIN® 90

(zinc, copper, manganese, and selenium injection)

Before using this drug, read package insert for full prescribing information.

Determine accurate body weights prior to treatment. Administer subcutaneously under the loose skin of the middle of the side of the neck per the following dosages depending on age and bodyweight of the cattle:

Cattle up to 1 year, 1 mL/100 lb bodyweight
Cattle from 1-2 years, 1 mL/150 lb bodyweight
Cattle over 2 years, 1 mL/200 lb bodyweight

To be administered as a single dose.

MULTIMIN® 90 is to be given subcutaneously (under the skin) ONLY.

The maximum volume per injection site is 7 mL. Use standard aseptic procedures during administration to reduce the risk of injection site abscesses or lesions. Ensure there are at least 4 inches between injection sites for MULTIMIN® 90 and other injection sites.

MULTIMIN® 90 is intended as a single dose product. Allow a minimum of 30 days before considering repeat dosing. Additional zinc, copper, manganese, or selenium products should not be administered at the same time.

Use within 28 days of first puncture of the vial and puncture a maximum of 15 times. If more than 15 punctures are anticipated, the use of multi-dosing equipment is recommended. When using a draw-off spike or needle with bore diameter larger than 16 gauge, discard any product remaining in the vial immediately after use.

MULTIMIN® 90 is intended as a single dose product. Allow a minimum of 30 days before considering repeat dosing. Additional zinc, copper, manganese, or selenium products should not be administered at the same time.
Use within 28 days of first puncture of the vial and puncture a maximum of 15 times. If more than 15 punctures are anticipated, the use of multi-dosing equipment is recommended. When using a draw-off spike or needle with bore diameter larger than 16 gauge, discard any product remaining in the vial immediately after use.

STORAGE, HANDLING AND DISPOSAL
Store between 15ºC and 30ºC (59ºF and 86ºF)

CONTRAINDICATIONS
Do not use MULTIMIN® 90 (zinc, copper, manganese, and selenium injection) concurrently with other injectable selenium and copper products.
Do not use MULTIMIN® 90 concurrently with selenium or copper boluses.

User Safety Warnings
Not for use in humans. Keep out of reach of children. Do not allow children access to used or empty syringes. Wash hands after use.

This product is highly concentrated in zinc, copper, manganese, and selenium. Due to a potential risk of zinc, copper, manganese, and selenium toxicity, care should be taken when handling the product to avoid accidental self-injection. Symptoms of exposure to zinc, copper, manganese, and selenium include aches, chills, nausea, vomiting, diarrhea, tachycardia, epigastric pain, tremors, and irritability.

In case of accidental self-injection or ingestion, SEEK IMMEDIATE MEDICAL ATTENTION and take the vial with you.
To obtain a Safety Data Sheet, contact Multimin North America, Inc. at 970-372-2302.

Animal Safety Warnings and Precautions
Selenium and copper are toxic if administered in excess. MULTIMIN® 90 may cause clinical signs associated with copper toxicity or selenium toxicity, including death, if overdosed or used in conjunction with excessive dietary levels of copper and selenium or other selenium or copper products. Additional zinc, copper, manganese, or selenium products should not be administered at the same time. Do not use concurrently with other injectable selenium and copper products. Do not use concurrently with selenium or copper boluses.
MULTIMIN® 90 may cause injection site swelling that appears on the day of injection and resolves by 2 days later. MULTIMIN® 90 may cause induration at the injection site that appears the day of injection and may persist for at least 14 days post-injection. These reactions may result in trim loss of edible tissue at slaughter.
Do not use in cases of known hypersensitivity to the active ingredients or to any of the excipients. Do not use in emaciated cattle with a body condition score of 1 on a 5-point scale in dairy or 1-3 on a 9-point scale in beef.
Do not use during the first trimester of pregnancy because safety has not been evaluated. Do not use in pre-ruminant calves because safety has not been evaluated.

Lot No:

Exp Date:

MULTIMIN® 90
(zinc, copper, manganese, and selenium injection)

A sterile solution for subcutaneous injection containing 60 mg/mL zinc, 15 mg/mL copper, 10 mg/mL manganese, and 5 mg/mL selenium.

Caution: Federal law restricts this drug to use by or on the order of a licensed veterinarian.

Approved by FDA under NADA # 141-582

NET CONTENTS: 500 mL

INDICATIONS FOR USE
To provide a supplemental source of zinc, copper, manganese, and selenium in cattle. Not for use in pregnant cows and heifers during their first trimester because reproductive safety testing has not been done in these animals. Do not use in beef calves less than 2 months of age, dairy calves, and veal calves because safety has not been established.

ACTIVE INGREDIENTS:
Zinc 60 mg/mL (as zinc oxide)
Copper 15 mg/mL (as copper carbonate)
Manganese 10 mg/mL (as manganese carbonate)
Selenium 5 mg/mL (as sodium selenite)

INACTIVE INGREDIENTS:
Edetic acid 399.74 mg/mL
Sodium hydroxide 106.9 mg/mL
Benzyl alcohol 10.4 mg/mL (as preservative)

Withdrawal Periods
Cattle must not be slaughtered for human food consumption within 14 days of the last treatment. No milk discard time is required when used according to labeling.

MANUFACTURED FOR:MULTIMIN NORTH AMERICA,INC.
2809 East Harmony Rd. Suite 190, Fort Collins, CO 80528
Manufactured by: Nova-Tech, Inc.,
4705 Gold Core Rd., Grand Island, NE, 68801

U.S. Patent: www.axiota.com/patent
Made in Ireland

NDC#49920-006-05